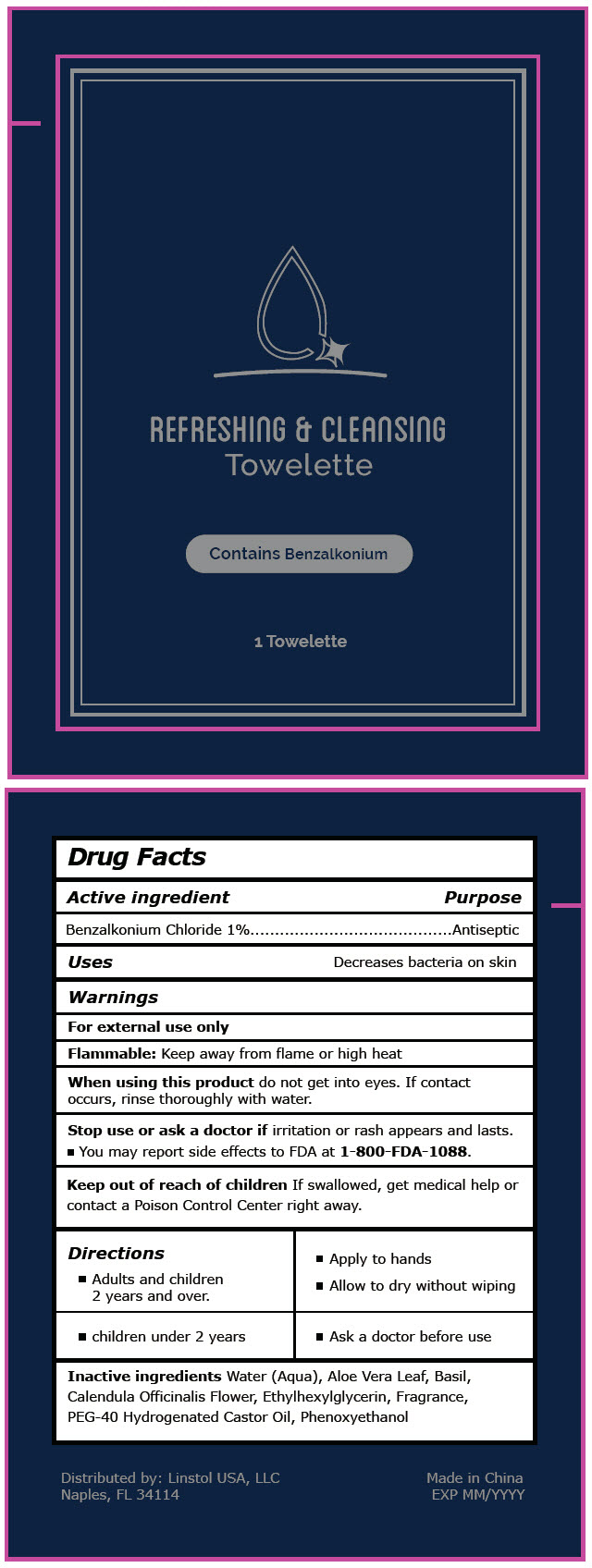 DRUG LABEL: Linstol Refreshing and Cleaning Towelette
NDC: 76982-8885 | Form: CLOTH
Manufacturer: Linstol USA, LLC
Category: otc | Type: HUMAN OTC DRUG LABEL
Date: 20221221

ACTIVE INGREDIENTS: BENZALKONIUM CHLORIDE 10 mg/1 mL
INACTIVE INGREDIENTS: WATER; ALOE VERA LEAF; BASIL; CALENDULA OFFICINALIS FLOWER; ETHYLHEXYLGLYCERIN; FRAGRANCE LAVENDER & CHIA F-153480; POLYOXYL 40 HYDROGENATED CASTOR OIL; PHENOXYETHANOL

Linstol Refreshing & Cleaning Towelette

Drug Facts

Active ingredient

Benzalkonium Chloride 1%

Purpose

Antiseptic

Uses

Decreases bacteria on skin

Warnings

For external use only

Flammable: Keep away from flame or high heat

When using this product do not get into eyes. If contact occurs, rinse thoroughly with water.

Stop use or ask a doctor if irritation or rash appears and lasts.

QUESTIONS

- You may report side effects to FDA at 1-800-FDA-1088.

Keep out of reach of children

If swallowed, get medical help or contact a Poison Control Center right away.

Directions

- Adults and children 2 years and over.

- Apply to hands
- Allow to dry without wiping

- children under 2 years

- Ask a doctor before use

Inactive ingredients

Water (Aqua), Aloe Vera Leaf, Basil, Calendula Officinalis Flower, Ethylhexylglycerin, Fragrance, PEG-40 Hydrogenated Castor Oil, Phenoxyethanol

Distributed by: Linstol USA, LLC
Naples, FL 34114

PRINCIPAL DISPLAY PANEL - 1 Towelette Packet

REFRESHING & CLEANSING
Towelette

Contains Benzalkonium

1 Towelette